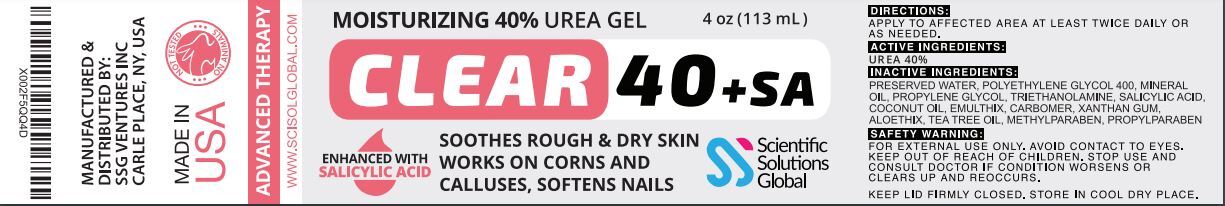 DRUG LABEL: Clear 40 Plus SA
NDC: 81376-232 | Form: GEL
Manufacturer: SSG Ventures Inc
Category: otc | Type: HUMAN OTC DRUG LABEL
Date: 20210427

ACTIVE INGREDIENTS: UREA 40 g/113 g; SALICYLIC ACID 6.5 g/113 g
INACTIVE INGREDIENTS: ALOE VERA LEAF; CARBOXYPOLYMETHYLENE; XANTHAN GUM; MINERAL OIL; COCONUT OIL; WATER; TRIDECETH-10; TEA TREE OIL; PROPYLENE GLYCOL

Clear 40 Plus SA

PACKAGE LABEL

ACTIVE INGREDIENTS:

UREA 40%, SALICYLIC ACID 2%, TEA TREE OIL, ALOE VERA

PURPOSE

SOOTHES ROUGH & DRY SKIN

HEALS CORNS & CALLOUSES

INDICATIONS AND USAGE

SOOTHES ROUGH & DRY SKIN

SAFE HANDLING WARNING

FOR EXTERNAL USE ONLY. AVOID CONTACT TO EYES.

KEEP OUT OF REACH OF CHILDREN. STOP USE AND CONSULT DOCTOR IF CONDITION WORSENS OR CLEARS UP AND REOCCURS.

KEEP LID FIRMLY CLOSED. STORE IN COOL DRY PLACE.

KEEP OUT OF REACH OF CHILDREN.

INSTRUCTIONS FOR USE

APPLY TO AFFECTED AREA AT LEAST TWICE DAILY OR AS NEEDED.USE CONTINUOUSLY FOR 2-3 WEEKS FOR OPTIMAL RESULTS.

INACTIVE INGREDIENT

CARBOMER, XANTHAN GUM, MINERAL OIL, PROPYLENE GLYCOL,EMULSIFIERS, TRIETHANOLAMINE

STORAGE AND HANDLING

KEEP LID FIRMLY CLOSED. STORE IN COOL DRY PLACE.

OTHER SAFETY INFORMATION

ENHANCED WITH TEA TREE OIL & ALOE VERA

DOSAGE AND ADMINISTRATION

APPLY TO AFFECTED AREA AT LEAST TWICE DAILY OR AS NEEDED.USE CONTINUOUSLY FOR 2-3 WEEKS FOR OPTIMAL RESULTS.

WARNINGS

FOR EXTERNAL USE ONLY. AVOID CONTACT TO EYES. STOP USE AND CONSULT DOCTOR IF CONDITION WORSENS OR CLEARS UP AND REOCCURS.